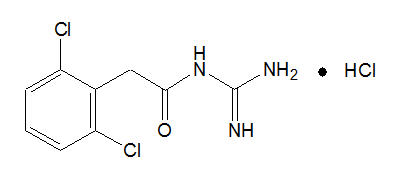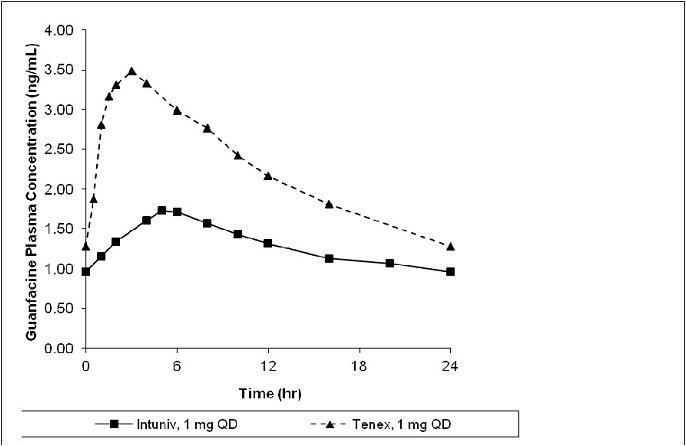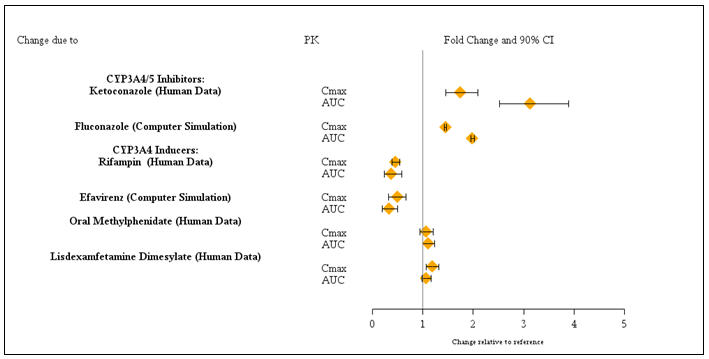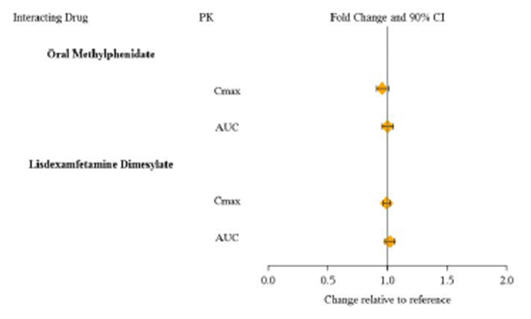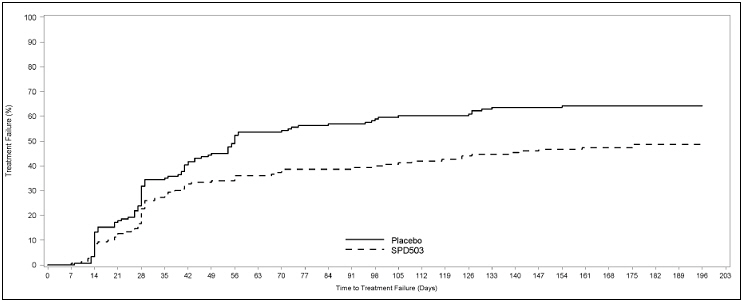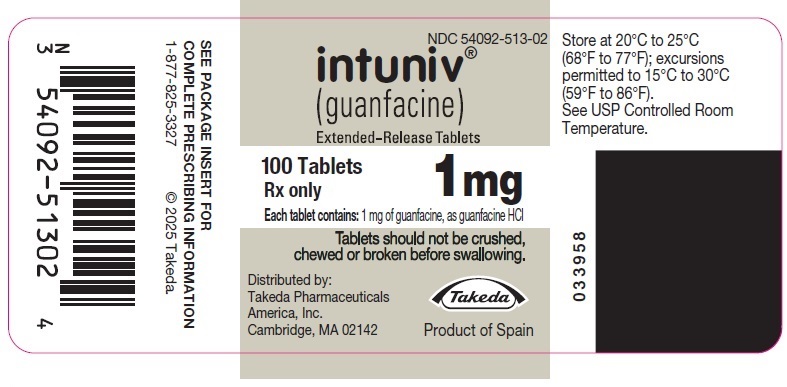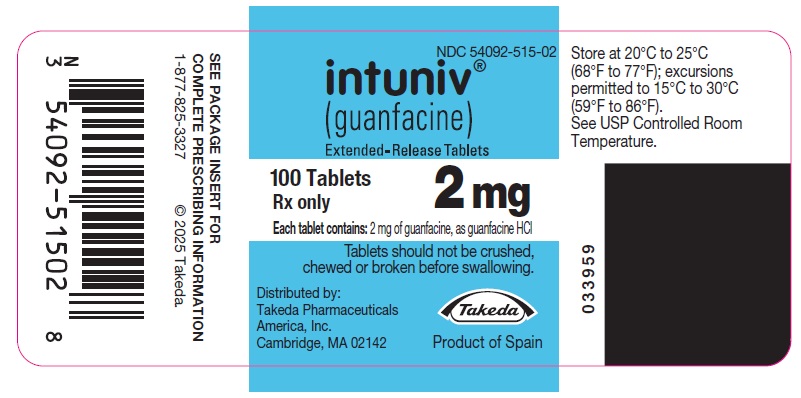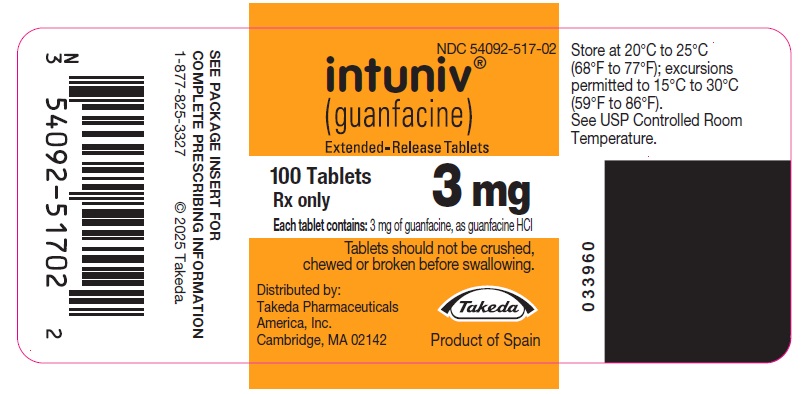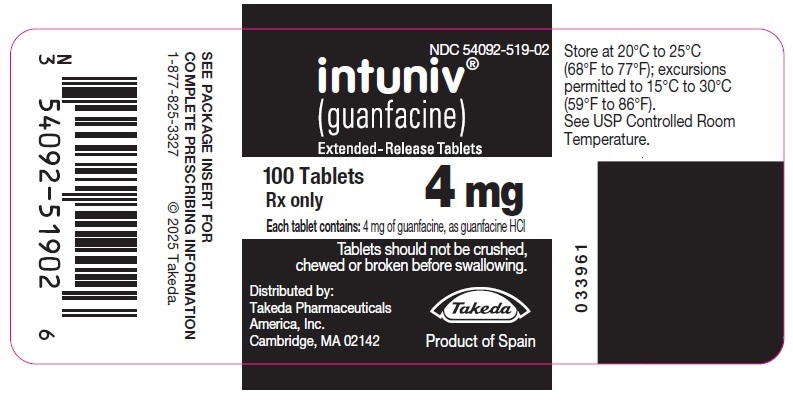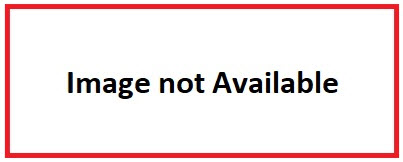 DRUG LABEL: Intuniv
NDC: 54092-513 | Form: TABLET, EXTENDED RELEASE
Manufacturer: Takeda Pharmaceuticals America, Inc.
Category: prescription | Type: HUMAN PRESCRIPTION DRUG LABEL
Date: 20250623

ACTIVE INGREDIENTS: GUANFACINE HYDROCHLORIDE 1 mg/1 1
INACTIVE INGREDIENTS: HYPROMELLOSE 2208 (15000 MPA.S); LACTOSE MONOHYDRATE; POVIDONE, UNSPECIFIED; CROSPOVIDONE (120 .MU.M); METHACRYLIC ACID - METHYL METHACRYLATE COPOLYMER (1:1); MICROCRYSTALLINE CELLULOSE; GLYCERYL DIBEHENATE; FUMARIC ACID

HIGHLIGHTS OF PRESCRIBING INFORMATION

These highlights do not include all the information needed to use INTUNIV® safely and effectively. See full prescribing information for INTUNIV.
INTUNIV® (guanfacine) extended-release tablets, for oral use
Initial U.S. Approval: 1986

1 INDICATIONS AND USAGE

INTUNIV is a central alpha2A-adrenergic receptor agonist indicated for the treatment of Attention Deficit Hyperactivity Disorder (ADHD) as monotherapy and as adjunctive therapy to stimulant medications (1,14).

2 DOSAGE AND ADMINISTRATION

- Recommended dose: 1 mg to 7 mg (0.05 to 0.12 mg/kg target weight based dose range) once daily in the morning or evening based on clinical response and tolerability (2.2).
- Begin at a dose of 1 mg once daily and adjust in increments of no more than 1 mg/week (2.2).
- Do not crush, chew or break tablets before swallowing (2.1).
- Do not administer with high-fat meals, because of increased exposure (2.1).
- Do not substitute for immediate-release guanfacine tablets on a mg-per-mg basis, because of differing pharmacokinetic profiles (2.3).
- If switching from immediate-release guanfacine, discontinue that treatment and titrate with INTUNIV as directed (2.3).
- When discontinuing, taper the dose in decrements of no more than 1 mg every 3 to 7 days to avoid rebound hypertension (2.5).

3 DOSAGE FORMS AND STRENGTHS

Extended-release tablets: 1 mg, 2 mg, 3 mg, and 4 mg (3)

4 CONTRAINDICATIONS

History of hypersensitivity to INTUNIV, its inactive ingredients, or other products containing guanfacine (4).

5 WARNINGS AND PRECAUTIONS

- Hypotension, bradycardia, syncope: Titrate slowly and monitor vital signs frequently in patients at risk for hypotension, heart block, bradycardia, syncope, cardiovascular disease, vascular disease, cerebrovascular disease or chronic renal failure. Measure heart rate and blood pressure prior to initiation of therapy, following dose increases, and periodically while on therapy. Avoid concomitant use of drugs with additive effects unless clinically indicated. Advise patients to avoid becoming dehydrated or overheated (5.1).
- Sedation and somnolence: Occur commonly with INTUNIV. Consider the potential for additive sedative effects with CNS depressant drugs. Caution patients against operating heavy equipment or driving until they know how they respond to INTUNIV (5.2).
- Cardiac Conduction Abnormalities: May worsen sinus node dysfunction and atrioventricular (AV) block, especially in patients taking other sympatholytic drugs. Titrate slowly and monitor vital signs frequently (5.3).
- Rebound Hypertension: Abrupt discontinuation of INTUNIV can lead to clinically significant and persistent rebound hypertension. Subsequent hypertensive encephalopathy was also reported. To minimize the risk of rebound hypertension upon discontinuation, the total daily dose of INTUNIV should be tapered in decrements of no more than 1 mg every 3 to 7 days (5.4).

6 ADVERSE REACTIONS

Most common adverse reactions (≥5% and at least twice placebo rate) in fixed-dose monotherapy ADHD trials in children and adolescents (6 to 17 years): hypotension, somnolence, fatigue, nausea, and lethargy (6.1)

Flexible dose-optimization ADHD trials in children (6 to 12 years) and adolescents (13 to 17 years): somnolence, hypotension, abdominal pain, insomnia, fatigue, dizziness, dry mouth, irritability, nausea, vomiting, and bradycardia (6.1).

Adjunctive treatment to psychostimulant ADHD trial in children and adolescents (6 to 17 years): somnolence, fatigue, insomnia, dizziness, and abdominal pain (6.1).
To report SUSPECTED ADVERSE REACTIONS, contact Takeda Pharmaceuticals at 1-877-TAKEDA-7 (1-877-825-3327) or FDA at 1-800-FDA-1088 or www.fda.gov/medwatch.

7 DRUG INTERACTIONS

- Strong and moderate CYP3A4 inhibitors increase guanfacine exposure. Decrease INTUNIV to 50% of target dosage when coadministered with strong and moderate CYP3A4 inhibitors (2.7).
- Strong and moderate CYP3A4 inducers decrease guanfacine exposure. Based on patient response, consider titrating INTUNIV dosage up to double the target dosage over 1 to 2 weeks (2.7).

FULL PRESCRIBING INFORMATION

1 INDICATIONS AND USAGE

INTUNIV® is indicated for the treatment of Attention Deficit Hyperactivity Disorder (ADHD) as monotherapy and as adjunctive therapy to stimulant medications [see Clinical Studies (14)].

2 DOSAGE AND ADMINISTRATION

2.1 General Instruction for Use

Swallow tablets whole. Do not crush, chew, or break tablets because this will increase the rate of guanfacine release. Do not administer with high fat meals, due to increased exposure.

2.2 Dose Selection

Take INTUNIV orally once daily, either in the morning or evening, at approximately the same time each day. Begin at a dose of 1 mg/day, and adjust in increments of no more than 1 mg/week.

In monotherapy clinical trials, there was dose- and exposure-related clinical improvement as well as risks for several clinically significant adverse reactions (hypotension, bradycardia, sedative events). To balance the exposure-related potential benefits and risks, the recommended target dose range depending on clinical response and tolerability for INTUNIV is 0.05 to 0.12 mg/kg/day (total daily dose between 1 to 7 mg) (See Table 1).

Table 1: Recommended Target Dose Range for Therapy with INTUNIV
Weight | Target dose range (0.05 to 0.12 mg/kg/day)
25 to 33.9 kg | 2 to 3 mg/day
34 to 41.4 kg | 2 to 4 mg/day
41.5 to 49.4 kg | 3 to 5 mg/day
49.5 to 58.4 kg | 3 to 6 mg/day
58.5 to 91 kg | 4 to 7 mg/day
>91 kg | 5 to 7 mg/day
Doses above 4 mg/day have not been evaluated in children (ages 6 to 12 years) and doses above 7 mg/day have not been evaluated in adolescents (ages 13 to 17 years)

In the adjunctive trial which evaluated INTUNIV treatment with psychostimulants, the majority of patients reached optimal doses in the 0.05 to 0.12 mg/kg/day range. Doses above 4 mg/day have not been studied in adjunctive trials.

2.3 Switching from Immediate-Release Guanfacine to INTUNIV

If switching from immediate-release guanfacine, discontinue that treatment, and titrate with INTUNIV following above recommended schedule.

Do not substitute for immediate-release guanfacine tablets on a milligram-per-milligram basis, because of differing pharmacokinetic profiles. INTUNIV has significantly reduced Cmax (60% lower), bioavailability (43% lower), and a delayed Tmax (3 hours later) compared to those of the same dose of immediate-release guanfacine [see Clinical Pharmacology (12.3)].

2.4 Maintenance Treatment

Pharmacological treatment of ADHD may be needed for extended periods. Healthcare providers should periodically re-evaluate the long-term use of INTUNIV, and adjust weight-based dosage as needed. The majority of children and adolescents reach optimal doses in the 0.05 to 0.12 mg/kg/day range. Doses above 4 mg/day have not been evaluated in children (ages 6 to 12 years) and above 7 mg/day have not been evaluated in adolescents (ages 13 to 17 years) [see Clinical Studies (14)].

2.5 Discontinuation of Treatment

Following discontinuation of INTUNIV, patients may experience increases in blood pressure and heart rate [see Warnings and Precautions (5.4) and Adverse Reactions (6)]. Patients/caregivers should be instructed not to discontinue INTUNIV without consulting their health care provider. Monitor blood pressure and pulse when reducing the dose or discontinuing the drug. Taper the daily dose in decrements of no more than 1 mg every 3 to 7 days to minimize the risk of rebound hypertension.

2.6 Missed Doses

When reinitiating patients to the previous maintenance dose after two or more missed consecutive doses, consider titration based on patient tolerability.

2.7 Dosage Adjustment with Concomitant Use of Strong and Moderate CYP3A4 Inhibitors or Inducers

Dosage adjustments for INTUNIV are recommended with concomitant use of strong and moderate CYP3A4 inhibitors (e.g., ketoconazole), or CYP3A4 inducers (e.g., carbamazepine) (Table 2) [see Drug Interactions (7)].

Table 2: INTUNIV Dosage Adjustments for Patients Taking Concomitant CYP3A4 Inhibitors or Inducers
 | Clinical Scenarios
 | Starting INTUNIV while currently on a CYP3A4 modulator | Continuing INTUNIV while adding a CYP3A4 modulator | Continuing INTUNIV while stopping a CYP3A4 modulator
CYP3A4 Strong and moderate Inhibitors | Decrease INTUNIV dosage to half the recommended level. (see Table 1) | Decrease INTUNIV dosage to half the recommended level. (see Table 1) | Increase INTUNIV dosage to recommended level. (see Table 1)
CYP3A4 Strong and moderate Inducers | Consider increasing INTUNIV dosage up to double the recommended level. (see Table 1) | Consider increasing INTUNIV dosage up to double the recommended level over 1 to 2 weeks. (see Table 1) | Decrease INTUNIV dosage to recommended level over 1 to 2 weeks. (see Table 1)

3 DOSAGE FORMS AND STRENGTHS

1 mg, 2 mg, 3 mg, and 4 mg extended-release tablets

4 CONTRAINDICATIONS

INTUNIV is contraindicated in patients with a history of a hypersensitivity reaction to INTUNIV or its inactive ingredients, or other products containing guanfacine. Rash and pruritus have been reported.

5 WARNINGS AND PRECAUTIONS

5.1 Hypotension, Bradycardia, and Syncope

Treatment with INTUNIV can cause dose-dependent decreases in blood pressure and heart rate. Decreases were less pronounced over time of treatment. Orthostatic hypotension and syncope have been reported [see Adverse Reactions (6.1)].

Measure heart rate and blood pressure prior to initiation of therapy, following dose increases, and periodically while on therapy. Titrate INTUNIV slowly in patients with a history of hypotension, and those with underlying conditions that may be worsened by hypotension and bradycardia; e.g., heart block, bradycardia, cardiovascular disease, vascular disease, cerebrovascular disease, or chronic renal failure. In patients who have a history of syncope or may have a condition that predisposes them to syncope, such as hypotension, orthostatic hypotension, bradycardia, or dehydration, advise patients to avoid becoming dehydrated or overheated. Monitor blood pressure and heart rate, and adjust dosages accordingly in patients treated concomitantly with antihypertensives or other drugs that can reduce blood pressure or heart rate or increase the risk of syncope.

5.2 Sedation and Somnolence

Somnolence and sedation were commonly reported adverse reactions in clinical studies [see Adverse Reactions (6.1)]. Before using INTUNIV with other centrally active depressants, consider the potential for additive sedative effects. Caution patients against operating heavy equipment or driving until they know how they respond to treatment with INTUNIV. Advise patients to avoid use with alcohol.

5.3 Cardiac Conduction Abnormalities

The sympatholytic action of INTUNIV may worsen sinus node dysfunction and atrioventricular (AV) block, especially in patients taking other sympatholytic drugs. Titrate INTUNIV slowly and monitor vital signs frequently in patients with cardiac conduction abnormalities or patients concomitantly treated with other sympatholytic drugs.

5.4 Rebound Hypertension

In post marketing experience, abrupt discontinuation of INTUNIV has resulted in clinically significant and persistent rebound hypertension above baseline levels and increases in heart rate. Hypertensive encephalopathy has also been reported in association with rebound hypertension with both INTUNIV and immediate release guanfacine [see Adverse Reactions (6.2)]. In these cases, high-dosage guanfacine was discontinued; concomitant stimulant use was also reported, which may potentially increase hypertensive response upon abrupt discontinuation of guanfacine. Children commonly have gastrointestinal illnesses that lead to vomiting, and a resulting inability to take medications, so they may be especially at risk for rebound hypertension.

To minimize the risk of rebound hypertension upon discontinuation, the total daily dose of INTUNIV should be tapered in decrements of no more than 1 mg every 3 to 7 days [see Dosage and Administration (2.5)]. Blood pressure and heart rate should be monitored when reducing the dose or discontinuing INTUNIV. If abrupt discontinuation occurs (especially with concomitant stimulant use), patients should be closely followed for rebound hypertension.

6 ADVERSE REACTIONS

The following serious adverse reactions are described elsewhere in the labeling:

- Hypotension, bradycardia, and syncope [see Warnings and Precautions (5.1)]
- Sedation and somnolence [see Warnings and Precautions (5.2)]
- Cardiac conduction abnormalities [see Warnings and Precautions (5.3)]
- Rebound Hypertension [see Warnings and Precautions (5.4)]

6.1 Clinical Trials Experience

Because clinical trials are conducted under widely varying conditions, adverse reaction rates observed in the clinical trials of a drug cannot be directly compared to rates in the clinical trials of another drug and may not reflect the rates observed in practice.

The data described below reflect clinical trial exposure to INTUNIV in 2,825 patients. This includes 2,330 patients from completed studies in children and adolescents, ages 6 to 17 years and 495 patients in completed studies in adult healthy volunteers.

The mean duration of exposure of 446 patients that previously participated in two 2-year, open-label long-term studies was approximately 10 months.

Fixed Dose Trials

Table 3: Percentage of Patients Experiencing Most Common (≥5% and at least twice the rate for placebo) Adverse Reactions in Fixed Dose Studies 1 and 2
 |  | INTUNIV (mg)
Adverse Reaction Term | Placebo (N=149) | 1 mg [The lowest dose of 1 mg used in Study 2 was not randomized to patients weighing more than 50 kg.] (N=61) | 2 mg (N=150) | 3 mg (N=151) | 4 mg (N=151) | All Doses of INTUNIV (N=513)
Somnolence [The somnolence term includes somnolence, sedation, and hypersomnia.] | 11% | 28% | 30% | 38% | 51% | 38%
Fatigue | 3% | 10% | 13% | 17% | 15% | 14%
Hypotension [The hypotension term includes hypotension, diastolic hypotension, orthostatic hypotension, blood pressure decreased, blood pressure diastolic decreased, blood pressure systolic decreased).] | 3% | 8% | 5% | 7% | 8% | 7%
Dizziness | 4% | 5% | 3% | 7% | 10% | 6%
Lethargy | 3% | 2% | 3% | 8% | 7% | 6%
Nausea | 2% | 7% | 5% | 5% | 6% | 6%
Dry mouth | 1% | 0% | 1% | 6% | 7% | 4%

Table 4: Adverse Reactions Leading to Discontinuation (≥2% for all doses of INTUNIV and >rate than in placebo) in Fixed Dose Studies 1 and 2
 |  |  | INTUNIV (mg)
Adverse Reaction Term | Placebo (N=149) |  | 1 mg [The lowest dose of 1 mg used in Study 2 was not randomized to patients weighing more than 50 kg.] (N=61) |  | 2 mg (N=150) |  | 3 mg (N=151) |  | 4 mg (N=151) |  | All Doses of INTUNIV (N=513)
 | n | (%) | n | (%) | n | (%) | n | (%) | n | (%) | n | (%)
Total patients | 4 | (3%) | 2 | (3%) | 10 | (7%) | 15 | (10%) | 27 | (18%) | 54 | (11%)
Somnolence [The somnolence term includes somnolence, sedation, and hypersomnia.] | 1 | (1%) | 2 | (3%) | 5 | (3%) | 6 | (4%) | 17 | (11%) | 30 | (6%)
Fatigue | 0 | (0%) | 0 | (0%) | 2 | (1%) | 2 | (1%) | 4 | (3%) | 8 | (2%)
Adverse reactions leading to discontinuation in ≥2% in any dose group but did not meet this criteria in all doses combined: hypotension (hypotension, diastolic hypotension, orthostatic hypotension, blood pressure decreased, blood pressure diastolic decreased, blood pressure systolic decreased), headache, and dizziness.

Table 5: Other Common Adverse Reactions (≥2% for all doses of INTUNIV and >rate than in placebo) in Fixed Dose Studies 1 and 2
 |  | INTUNIV (mg)
Adverse Reaction Term | Placebo (N=149) | 1 mg [The lowest dose of 1 mg used in Study 2 was not randomized to patients weighing more than 50 kg.] (N=61) | 2 mg (N=150) | 3 mg (N=151) | 4 mg (N=151) | All Doses of INTUNIV (N=513)
Headache | 19% | 26% | 25% | 16% | 28% | 23%
Abdominal Pain [The abdominal pain term includes abdominal pain, abdominal pain lower, abdominal pain upper, and abdominal tenderness.] | 9% | 10% | 7% | 11% | 15% | 11%
Decreased Appetite | 4% | 5% | 4% | 9% | 6% | 6%
Irritability | 4% | 5% | 8% | 3% | 7% | 6%
Constipation | 1% | 2% | 2% | 3% | 4% | 3%
Nightmare [The nightmare term includes abnormal dreams, nightmare, and sleep terror.] | 0% | 0% | 0% | 3% | 4% | 2%
Enuresis [The enuresis term includes enuresis, nocturia, and urinary incontinence.] | 1% | 0% | 1% | 3% | 2% | 2%
Affect Lability [The affect lability term includes affect lability and mood swings.] | 1% | 2% | 1% | 3% | 1% | 2%
Adverse reactions ≥2% for all doses of INTUNIV and >rate in placebo in any dose group but did not meet this criteria in all doses combined: insomnia (insomnia, initial insomnia, middle insomnia, terminal insomnia, sleep disorder), vomiting, diarrhea, abdominal/stomach discomfort (abdominal discomfort, epigastric discomfort, stomach discomfort), rash (rash, rash generalized, rash papular), dyspepsia, increased weight, bradycardia (bradycardia, sinus bradycardia), asthma (asthma, bronchospasm, wheezing), agitation, anxiety (anxiety, nervousness), sinus arrhythmia, blood pressure increased (blood pressure increased, blood pressure diastolic increased), and first degree atrioventricular block.

Monotherapy Flexible Dose Trials

Table 6: Percentage of Patients Experiencing Most Common (≥5% and at least twice the rate for placebo) Adverse Reactions in the Monotherapy Flexible Dose Study 4
 |  | INTUNIV
Adverse Reaction Term | Placebo (N=112) | AM (N=107) | PM (N=114) | All Doses of INTUNIV (N=221)
Somnolence [The somnolence term includes somnolence, sedation, and hypersomnia.] | 15% | 57% | 54% | 56%
Abdominal Pain [The abdominal pain term includes abdominal pain, abdominal pain lower, abdominal pain upper, and abdominal tenderness] | 7% | 8% | 19% | 14%
Fatigue | 3% | 10% | 11% | 11%
Irritability | 3% | 7% | 7% | 7%
Nausea | 1% | 6% | 5% | 5%
Dizziness | 3% | 6% | 4% | 5%
Vomiting | 2% | 7% | 4% | 5%
Hypotension [The hypotension term includes hypotension, diastolic hypotension, orthostatic hypotension, blood pressure decreased, blood pressure diastolic decreased, blood pressure systolic decreased).] | 0% | 6% | 4% | 5%
Decreased Appetite | 3% | 6% | 3% | 4%
Enuresis [The enuresis term includes enuresis, nocturia, and urinary incontinence.] | 1% | 2% | 5% | 4%

Table 7: Adverse Reactions Leading to Discontinuation (≥2% for all doses of INTUNIV and >rate than in placebo) in Monotherapy Flexible Dose Study 4
 |  |  | INTUNIV
Adverse Reaction Term | Placebo (N=112) |  | AM (N=107) |  | PM (N=114) |  | All Doses of INTUNIV (N=221)
 | n | (%) | n | (%) | n | (%) | n | (%)
Total patients | 0 | (0%) | 8 | (7%) | 7 | (6%) | 15 | (7%)
Somnolence [The somnolence term includes somnolence, sedation, and hypersomnia.] | 0 | (0%) | 4 | (4%) | 3 | (3%) | 7 | (3%)
Adverse reactions leading to discontinuation in ≥2% in any dose group but did not meet this criteria in all doses combined: fatigue

Table 8: Other Common Adverse Reactions (≥2% for all doses of INTUNIV and >rate than in placebo) in the Monotherapy Flexible Dose Study 4
 |  | INTUNIV
Adverse Reaction Term | Placebo (N=112) | AM (N=107) | PM (N=114) | All Doses of INTUNIV (N=221)
Headache | 11% | 18% | 16% | 17%
Insomnia [The insomnia term includes insomnia, initial insomnia, middle insomnia, terminal insomnia, and sleep disorder.] | 6% | 8% | 6% | 7%
Diarrhea | 4% | 4% | 6% | 5%
Lethargy | 0% | 4% | 3% | 3%
Constipation | 2% | 2% | 4% | 3%
Dry Mouth | 1% | 3% | 3% | 3%
Adverse reactions ≥2% for all doses of INTUNIV and >rate in placebo in any dose group but did not meet this criteria in all doses combined: affect lability (affect lability, mood swings), increased weight, syncope/loss of consciousness (loss of consciousness, presyncope, syncope), dyspepsia, tachycardia (tachycardia, sinus tachycardia), and bradycardia (bradycardia, sinus bradycardia).

Table 9: Percentage of Patients Experiencing Most Common (≥5% and at least twice the rate for placebo) Adverse Reactions in the Monotherapy Flexible Dose Study 5
Adverse Reaction Term | Placebo (N=155) | All Doses of INTUNIV (N=157)
Somnolence [The somnolence term includes somnolence, sedation, and hypersomnia.] | 23% | 54%
Insomnia [The insomnia term includes insomnia, initial insomnia, middle insomnia, terminal insomnia, and sleep disorder.] | 6% | 13%
Hypotension [The hypotension term includes hypotension, diastolic hypotension, orthostatic hypotension, blood pressure decreased, blood pressure diastolic decreased, blood pressure systolic decreased).] | 3% | 9%
Dry Mouth | 0% | 8%
Postural Dizziness | 2% | 5%
Bradycardia [The bradycardia term includes bradycardia and sinus bradycardia.] | 0% | 5%

There were no specific adverse reactions ≥2% in any treatment group that led to discontinuation in the monotherapy flexible dose study (Study 5).

Table 10: Other Common Adverse Reactions (≥2% for all doses of INTUNIV and >rate than in placebo) in the Monotherapy Flexible Dose Study 5
 |  | INTUNIV
Adverse Reaction Term | Placebo (N=155) | All Doses of INTUNIV (N=157)
Headache | 18% | 27%
Fatigue | 12% | 22%
Dizziness | 10% | 16%
Decreased Appetite | 14% | 15%
Abdominal Pain [The abdominal pain term includes abdominal pain, abdominal pain lower, abdominal pain upper, and abdominal tenderness.] | 8% | 12%
Irritability | 4% | 7%
Anxiety [The anxiety term includes anxiety and nervousness.] | 3% | 5%
Rash [The rash term includes rash, rash generalized, and rash papular.] | 1% | 3%
Constipation | 0% | 3%
Increased Weight | 2% | 3%
Abdominal/Stomach Discomfort [The abdominal/stomach discomfort term includes abdominal discomfort, epigastric discomfort, and stomach discomfort.] | 1% | 2%
Pruritus | 1% | 2%
Adverse reactions ≥2% for all doses of INTUNIV and >rate in placebo in any dose group but did not meet this criteria in all doses combined: nausea, diarrhea, vomiting, and depression (depressed mood, depression, depressive symptom).

Adjunctive Trial

Table 11: Percentage of Patients Experiencing Most Common (≥5% and at least twice the rate for placebo) Adverse Reactions in the Short-Term Adjunctive Study 3
 |  | INTUNIV + stimulant
Adverse Reaction Term | Placebo+ stimulant (N=153) | AM (N=150) | PM (N=152) | All Doses (N=302)
Somnolence [The somnolence term includes somnolence, sedation, and hypersomnia.] | 7% | 18% | 18% | 18%
Insomnia [The insomnia term includes insomnia, initial insomnia, middle insomnia, terminal insomnia, and sleep disorder.] | 6% | 10% | 14% | 12%
Abdominal Pain [The abdominal pain term includes abdominal pain, abdominal pain lower, abdominal pain upper, and abdominal tenderness.] | 3% | 8% | 12% | 10%
Fatigue | 3% | 12% | 7% | 10%
Dizziness | 4% | 10% | 5% | 8%
Decreased Appetite | 4% | 7% | 8% | 7%
Nausea | 3% | 3% | 7% | 5%

There were no specific adverse reactions ≥2% in any treatment group that led to discontinuation in the short-term adjunctive study (Study 3).

Table 12: Other Common Adverse Reactions (≥2% for all doses of INTUNIV and >rate than in placebo) in the Short-Term Adjunctive Study 3
 |  | INTUNIV + stimulant
Adverse Reaction Term | Placebo (N=153) | AM (N=150) | PM (N=152) | All Doses of INTUNIV (N=302)
Headache | 13% | 21% | 21% | 21%
Diarrhea | 1% | 4% | 3% | 4%
Hypotension [The hypotension term includes hypotension, diastolic hypotension, orthostatic hypotension, blood pressure decreased, blood pressure diastolic decreased, blood pressure systolic decreased.] | 0% | 4% | 2% | 3%
Constipation | 0% | 2% | 3% | 2%
Affect Lability [The affect lability term includes affect lability and mood swings.] | 1% | 3% | 2% | 2%
Dry Mouth | 0% | 1% | 3% | 2%
Bradycardia [The bradycardia term includes bradycardia and sinus bradycardia.] | 0% | 1% | 3% | 2%
Postural Dizziness | 0% | 1% | 3% | 2%
Rash [The rash term includes rash, rash generalized, and rash papular.] | 1% | 1% | 2% | 2%
Nightmare [The nightmare term includes abnormal dreams, nightmare, and sleep terror.] | 1% | 2% | 1% | 2%
Tachycardia [The tachycardia term includes tachycardia and sinus tachycardia.] | 1% | 2% | 1% | 2%
Adverse reactions ≥2% for all doses of INTUNIV and >rate in placebo in any dose group but did not meet this criteria in all doses combined: irritability, vomiting, asthma (asthma, bronchospasm, wheezing), and enuresis (enuresis, nocturia, urinary incontinence).

Effects on Blood Pressure and Heart Rate

In the monotherapy pediatric, short-term, controlled trials (Studies 1 and 2), the maximum mean changes from baseline in seated systolic blood pressure, diastolic blood pressure, and pulse were −5.4 mmHg, −3.4 mmHg, and −5.5 bpm, respectively, for all doses combined (generally one week after reaching target doses). For the respective fixed doses 1 mg/day, 2 mg/day, 3 mg/day, or 4 mg/day the maximum mean changes in seated systolic blood pressure were -4.3 mmHg, -5.5 mmHg, -5.4 mmHg, and -8.2 mmHg. For these respective fixed doses the maximum mean changes in seated diastolic blood pressure were -3.4 mmHg, -3.3 mmHg, -4.4 mmHg, and -5.4 mmHg. For these respective fixed doses the maximum mean changes in seated pulse were -4.8 bpm, -3.1 bpm, -6.5 bpm, and -8.6 bpm. Decreases in blood pressure and heart rate were usually modest and asymptomatic; however, hypotension and bradycardia can occur. Hypotension was reported as an adverse reaction for 7% of the INTUNIV group and 3% of the placebo group. This includes orthostatic hypotension, which was reported for 1% of the INTUNIV group and none in the placebo group. These findings were generally similar in the monotherapy flexible dose trials (Studies 4 and 5). In the adjunctive trial, hypotension (3%) and bradycardia (2%) were observed in patients treated with INTUNIV as compared to none in the placebo group. In long-term, open-label studies, (mean exposure of approximately 10 months), maximum decreases in systolic and diastolic blood pressure occurred in the first month of therapy. Decreases were less pronounced over time. Syncope occurred in 1% of pediatric patients in the clinical program. The majority of these cases occurred in the long-term, open-label studies.

Discontinuation of Treatment

Blood pressure and pulse may increase above baseline values following discontinuation of INTUNIV. In five studies of children and adolescents [see Clinical Studies (14)], increases in mean systolic and diastolic blood pressure averaging approximately 3 mmHg and increases in heart rate averaging 5 beats per minute above original baseline were observed upon discontinuation with tapering of INTUNIV. In a maintenance of efficacy study, increases in blood pressure and heart rate above baseline slowly diminished over the follow up period, which ranged between 3 and 26 weeks post final dose; the estimated average time to return to baseline was between six and twelve months. In this study, the increases in blood pressure and pulse were not considered serious or associated with adverse events. However, individuals may have larger increases than reflected by the mean changes.

In postmarketing experience, following abrupt discontinuation of INTUNIV, rebound hypertension and hypertensive encephalopathy have been reported [see Warnings and Precautions (5.4) and Adverse Reactions (6.2)].

Effects on Height, Weight, and Body Mass Index (BMI)

Patients taking INTUNIV demonstrated similar growth compared to normative data. Patients taking INTUNIV had a mean increase in weight of 0.5 kg compared to those receiving placebo over a comparable treatment period. Patients receiving INTUNIV for at least 12 months in open-label studies gained an average of 8 kg in weight and 8 cm (3 in) in height. The height, weight, and BMI percentile remained stable in patients at 12 months in the long-term studies compared to when they began receiving INTUNIV.

Other Adverse Reactions Observed in Clinical Studies

Table 13 includes additional adverse reactions observed in short-term, placebo-controlled and long-term, open-label clinical studies not included elsewhere in section 6.1, listed by organ system.

Table 13: Other adverse reactions observed in clinical studies
Body System | Adverse Reaction
Cardiac | Atrioventricular block
General | Asthenia, chest pain
Immune System Disorders | Hypersensitivity
Investigations | Increased alanine amino transferase
Nervous system | Convulsion
Renal | Increased urinary frequency
Vascular | Hypertension, pallor

6.2 Postmarketing Experience

The following adverse reactions have been identified during post-approval use of guanfacine. Because these reactions are reported voluntarily from a population of uncertain size, it is not always possible to reliably estimate their frequency or establish a causal relationship to drug exposure.

Less frequent, possibly guanfacine-related events observed in the post-marketing study and/or reported spontaneously, not included in section 6.1, include:

General: edema, malaise, tremor

Cardiovascular: palpitations, tachycardia, rebound hypertension, hypertensive encephalopathy

Central Nervous System: paresthesias, vertigo

Eye Disorders: blurred vision

Musculo-Skeletal System: arthralgia, leg cramps, leg pain, myalgia

Psychiatric: confusion, hallucinations

Reproductive System, Male: erectile dysfunction

Respiratory System: dyspnea

Skin and Appendages: alopecia, dermatitis, exfoliative dermatitis, pruritus, rash

Special Senses: alterations in taste

7 DRUG INTERACTIONS

Table 14 contains clinically important drug interactions with INTUNIV [see Clinical Pharmacology (12.3)].

Table 14: Clinically Important Drug Interactions: Effect of other Drugs on INTUNIV
Concomitant Drug Name or Drug Class | Clinical Rationale and Magnitude of Drug Interaction | Clinical Recommendation
Strong and moderate CYP3A4 inhibitors, e.g., ketoconazole, fluconazole | Guanfacine is primarily metabolized by CYP3A4 and its plasma concentrations can be significantly affected resulting in an increase in exposure | Consider dose reduction [see Dosage and administration (2.7)]
Strong and moderate CYP3A4 inducers, e.g., rifampin, efavirenz | Guanfacine is primarily metabolized by CYP3A4 and its plasma concentrations can be significantly affected resulting in a decrease in exposure | Consider dose increase [see Dosage and administration (2.7)]

8 USE IN SPECIFIC POPULATIONS

8.1 Pregnancy

Pregnancy Exposure Registry

There is a pregnancy exposure registry that monitors pregnancy outcomes in women exposed to ADHD medications, including INTUNIV, during pregnancy. Healthcare providers are encouraged to register patients by calling the National Pregnancy Registry for ADHD Medications at 1-866-961-2388.

Risk Summary

Available data with guanfacine over decades of use in pregnant women have not identified a drug-associated risk of major birth defects, miscarriage or adverse maternal or fetal outcomes. However, use of guanfacine in pregnant women over this time has been infrequent. In animal reproduction studies, rabbits and rats exposed to 3 and 4 times the maximum recommended human dose (MRHD), respectively, showed no adverse outcomes. However, higher doses were associated with reduced fetal survival and maternal toxicity (see Data).

The estimated background risk of major birth defects and miscarriage for the indicated population is unknown. All pregnancies have a background risk of birth defect, loss, or other adverse outcomes. In the U.S. general population, the estimated risk of major birth defects and miscarriage in clinically recognized pregnancies is 2% to 4% and 15% to 20%, respectively.

Data

Animal Data

Reproduction studies conducted in rats have shown that guanfacine crosses the placenta. However, administration of guanfacine to rabbits and rats during organogenesis at 3 (rabbit) and 4 (rat) times the MRHD of 0.12 mg/kg/day on a mg/m^2 basis resulted in no evidence of harm to the fetus. Higher doses (13.5 times the MRHD in both rabbits and rats) were associated with reduced fetal survival and maternal toxicity.

8.2 Lactation

Risk Summary

There are no data on the presence of guanfacine in human milk or the effects on the breastfed infant. The effects on milk production are also unknown. Guanfacine is present in the milk of lactating rats (see Data). If a drug is present in animal milk, it is likely that the drug will be present in human milk. If an infant is exposed to guanfacine through breastmilk, monitor for symptoms of hypotension and bradycardia such as sedation, lethargy, and poor feeding (see Clinical Considerations). The developmental and health benefits of breastfeeding should be considered along with the mother's clinical need for INTUNIV and any potential adverse effects on the breastfed child from INTUNIV or from the underlying maternal condition.

Clinical Considerations

Monitor breastfeeding infants exposed to guanfacine through breastmilk for sedation, lethargy, and poor feeding.

Data

Guanfacine was excreted in breast milk of lactating rats at a concentration comparable to that observed in blood, but slightly less than the concentration in plasma when administered following a single oral dose of 5 mg/kg. The concentration of drug in animal milk does not necessarily predict the concentration of drug in human milk.

8.4 Pediatric Use

Safety and efficacy of INTUNIV in pediatric patients less than 6 years of age have not been established. The efficacy of INTUNIV was studied for the treatment of ADHD in five controlled monotherapy clinical trials (up to 15 weeks in duration), one randomized withdrawal study and one controlled adjunctive trial with psychostimulants (8 weeks in duration) in children and adolescents ages 6 to 17 who met DSM-IV® criteria for ADHD [see Adverse Reactions (6) and Clinical Studies (14)].

Animal Data

In studies in juvenile rats, guanfacine alone produced a slight delay in sexual maturation in males and females at 2 to 3 times the maximum recommended human dose (MRHD). Guanfacine in combination with methylphenidate produced a slight delay in sexual maturation and decreased growth as measured by a decrease in bone length in males at a dose of guanfacine comparable to the MRHD and a dose of methylphenidate approximately 4 times the MRHD.

In a study where juvenile rats were treated with guanfacine alone from 7 to 59 days of age, development was delayed as indicated by a slight delay in sexual maturation and decreased body weight gain in males at 2 mg/kg/day and in females at 3 mg/kg/day. The No Adverse Effect Level (NOAEL) for delayed sexual maturation was 1 mg/kg/day, which is equivalent to the MRHD of 4 mg/day, on a mg/m^2 basis. The effects on fertility were not evaluated in this study.

In a study where juvenile rats were treated with guanfacine in combination with methylphenidate from 7 to 59 days of age, a decrease in ulna bone length and a slight delay in sexual maturation were observed in males given 1 mg/kg/day of guanfacine in combination with 50 mg/kg/day of methylphenidate. The NOAELs for these findings were 0.3 mg/kg of guanfacine in combination with 16 mg/kg/day of methylphenidate, which are equivalent to 0.3 and 1.4 times the MRHD of 4 mg/day and 54 mg/day for guanfacine and methylphenidate, respectively, on a mg/m^2 basis. These findings were not observed with guanfacine alone at 1 mg/kg/day or methylphenidate alone at 50 mg/kg/day.

8.5 Geriatric Use

The safety and efficacy of INTUNIV in geriatric patients have not been established.

8.6 Renal Impairment

It may be necessary to reduce the dosage in patients with significant impairment of renal function [see Clinical Pharmacology (12.3)].

8.7 Hepatic Impairment

It may be necessary to reduce the dosage in patients with significant impairment of hepatic function [see Clinical Pharmacology (12.3)].

9 DRUG ABUSE AND DEPENDENCE

9.1 Controlled Substance

INTUNIV is not a controlled substance and has no known potential for abuse or dependence.

10 OVERDOSAGE

Symptoms

Postmarketing reports of guanfacine overdosage indicate that hypotension, drowsiness, lethargy, and bradycardia have been observed following overdose. Initial hypertension may develop early and may be followed by hypotension. Similar symptoms have been described in voluntary reports to the American Association of Poison Control Center's National Poison Data System. Miosis of the pupils may be noted on examination. No fatal overdoses of guanfacine have been reported in published literature.

Treatment

Consult a Certified Poison Control Center by calling 1-800-222-1222 for up-to-date guidance and advice.

Management of INTUNIV overdose should include monitoring for and the treatment of initial hypertension, if that occurs, as well as hypotension, bradycardia, lethargy, and respiratory depression. Children and adolescents who develop lethargy should be observed for the development of more serious toxicity including coma, bradycardia, and hypotension for up to 24 hours, due to the possibility of delayed onset hypotension.

11 DESCRIPTION

INTUNIV is a once-daily, extended-release formulation of guanfacine hydrochloride (HCl) in a matrix tablet formulation for oral administration only. The chemical designation is N-amidino-2-(2,6-dichlorophenyl) acetamide monohydrochloride. The molecular formula is C9H9Cl2 N3O∙HCl corresponding to a molecular weight of 282.55 g/mol. The chemical structure is:

Guanfacine HCl is a white to off-white crystalline powder, sparingly soluble in water (approximately 1 mg/mL) and alcohol and slightly soluble in acetone. The only organic solvent in which it has relatively high solubility is methanol (>30 mg/mL). Each tablet contains guanfacine HCl equivalent to 1 mg, 2 mg, 3 mg, or 4 mg of guanfacine base. The tablets also contain hypromellose, methacrylic acid copolymer, lactose, povidone, crospovidone, microcrystalline cellulose, fumaric acid, and glyceryl behenate. In addition, the 3-mg and 4-mg tablets also contain green pigment blend PB-1763.

12 CLINICAL PHARMACOLOGY

12.1 Mechanism of Action

Guanfacine is a central alpha2A-adrenergic receptor agonist. Guanfacine is not a central nervous system (CNS) stimulant. The mechanism of action of guanfacine in ADHD is not known.

12.2 Pharmacodynamics

Guanfacine is a selective central alpha2A-adrenergic receptor agonist in that it has a 15 to 20 times higher affinity for this receptor subtype than for the alpha2B or alpha2C subtypes.

Guanfacine is a known antihypertensive agent. By stimulating central alpha2A-adrenergic receptors, guanfacine reduces sympathetic nerve impulses from the vasomotor center to the heart and blood vessels. This results in a decrease in peripheral vascular resistance and a reduction in heart rate.

In a thorough QT study, the administration of two dose levels of immediate-release guanfacine (4 mg and 8 mg) produced concentrations approximately 2 to 4 times the concentrations observed with the maximum recommended dose of INTUNIV of 0.12 mg/kg. Guanfacine was not shown to prolong the QTc interval to any clinically relevant extent.

12.3 Pharmacokinetics

Absorption and Distribution

Guanfacine is readily absorbed and approximately 70% bound to plasma proteins independent of drug concentration. After oral administration of INTUNIV the time to peak plasma concentration is approximately 5 hours in children and adolescents with ADHD.

Immediate-release guanfacine and INTUNIV have different pharmacokinetic characteristics; dose substitution on a milligram per milligram basis will result in differences in exposure.

A comparison across studies suggests that the Cmax is 60% lower and AUC0-∞ 43% lower, respectively, for INTUNIV compared to immediate-release guanfacine. Therefore, the relative bioavailability of INTUNIV to immediate-release guanfacine is 58%. The mean pharmacokinetic parameters in adults following the administration of INTUNIV 1 mg once daily and immediate-release guanfacine 1 mg once daily are summarized in Table 15.

Table 15: Comparison of Pharmacokinetics: INTUNIV vs. Immediate release Guanfacine in Adults
Parameter | INTUNIV 1 mg once daily (n=52) | Immediate-release guanfacine 1 mg once daily (n=12)
Cmax (ng/mL) | 1.0 ± 0.3 | 2.5 ± 0.6
AUC0-∞ (ng∙h/mL) | 32 ± 9 | 56 ± 15
tmax (h) | 6.0 (4.0 – 8.0) | 3.0 (1.5-4.0)
t½ (h) | 18 ± 4 | 16 ± 3
Note: Values are mean +/- SD, except for tmax which is median (range)

Figure 1: Comparison of Pharmacokinetics: INTUNIV vs. Immediate-release guanfacine in Adults

Exposure to guanfacine was higher in children (ages 6 to 12) compared to adolescents (ages 13 to 17) and adults. After oral administration of multiple doses of INTUNIV 4 mg, the Cmax was 10 ng/mL compared to 7 ng/mL and the AUC was 162 ng∙h/mL compared to 116 ng∙h/mL in children (ages 6 to 12) and adolescents (ages 13 to 17), respectively. These differences are probably attributable to the lower body weight of children compared to adolescents and adults.

The pharmacokinetics were affected by intake of food when a single dose of INTUNIV 4 mg was administered with a high-fat breakfast. The mean exposure increased (Cmax ~75% and AUC ~40%) compared to dosing in a fasted state.

Dose Proportionality

Following administration of INTUNIV in single doses of 1 mg, 2 mg, 3 mg, and 4 mg to adults, Cmax and AUC0-∞ of guanfacine were proportional to dose.

Metabolism and Elimination

In vitro studies with human liver microsomes and recombinant CYP's demonstrated that guanfacine was primarily metabolized by CYP3A4. In pooled human hepatic microsomes, guanfacine did not inhibit the activities of the major cytochrome P450 isoenzymes (CYP1A2, CYP2B6, CYP2C8, CYP2C9, CYP2C19, CYP2D6, or CYP3A4/5); guanfacine is also not an inducer of CYP3A, CYP1A2, and CYP2B6. Guanfacine is a substrate of CYP3A4/5 and exposure is affected by CYP3A4/5 inducers/inhibitors.

Guanfacine inhibits MATE1 and OCT1, but does not inhibit BSEP, MRP2, OATP1B1, OATP1B3, OAT1, OAT3, OCT2, or MATE2K. Guanfacine is a substrate of OCT1 and OCT2, but not BCRP, OATP1B1, OATP1B3, OAT1, OAT3, MATE1, or MATE2. Concomitant administration of guanfacine with OCT1 substrates might potentially increase the exposure of these OCT1 substrates.

Studies in Specific Populations

Renal Impairment

The impact of renal impairment on the pharmacokinetics of guanfacine in children was not assessed. In adult patients with impaired renal function, the cumulative urinary excretion of guanfacine and the renal clearance diminished as renal function decreased. In patients on hemodialysis, the dialysis clearance was about 15% of the total clearance. The low dialysis clearance suggests that the hepatic elimination (metabolism) increases as renal function decreases.

Hepatic Impairment

The impact of hepatic impairment on PK of guanfacine in children was not assessed. Guanfacine in adults is cleared both by the liver and the kidney, and approximately 50% of the clearance of guanfacine is hepatic [see Hepatic Impairment (8.7)].

Drug Interaction Studies

Guanfacine is primarily metabolized by CYP3A4 and its plasma concentrations can be affected significantly by CYP3A4 inhibitors or inducers (Figure 2).

Figure 2: Effect of Other Drugs on the Pharmacokinetics (PK) of INTUNIV

Guanfacine does not significantly affect exposures of methylphenidate and lisdexamfetamine when coadministered (Figure 3).

Figure 3: Effect of INTUNIV on the Pharmacokinetics (PK) of Other Drugs

13 NONCLINICAL TOXICOLOGY

13.1 Carcinogenesis, Mutagenesis, Impairment of Fertility

Carcinogenesis

No carcinogenic effect of guanfacine was observed in studies of 78 weeks in mice or 102 weeks in rats at doses up to 6.8 times the maximum recommended human dose of 0.12 mg/kg/day on a mg/m^2 basis.

Mutagenesis

Guanfacine was not genotoxic in a variety of test models, including the Ames test and an in vitro chromosomal aberration test; however, a marginal increase in numerical aberrations (polyploidy) was observed in the latter study.

Impairment of Fertility

No adverse effects were observed in fertility studies in male and female rats at doses up to 22 times the maximum recommended human dose on a mg/m^2 basis.

14 CLINICAL STUDIES

Efficacy of INTUNIV in the treatment of ADHD was established in children and adolescents (6 to 17 years) in:

- Five short-term, placebo-controlled monotherapy trials (Studies 1, 2, 4, 5, and 6).
- One short-term, placebo-controlled adjunctive trial with psychostimulants (Study 3).
- One long-term, placebo-controlled monotherapy maintenance trial (Study 7).

Studies 1 and 2: Fixed-dose INTUNIV Monotherapy

Study 1 (301 study) was a double-blind, placebo-controlled, parallel-group, fixed-dose study, in which efficacy of once daily dosing with INTUNIV (2 mg, 3 mg, and 4 mg) was evaluated for 5 weeks (n=345) in children and adolescents aged 6 to 17 years. Study 2 (304 study) was a double-blind, placebo-controlled, parallel-group, fixed-dose study, in which efficacy of once daily dosing with INTUNIV (1 mg, 2 mg, 3 mg, and 4 mg) was evaluated for 6 weeks (n=324) in children and adolescents aged 6 to 17 years. In both studies, randomized patients in 2 mg, 3 mg, and 4 mg dose groups were titrated to their target fixed dose, and continued on the same dose until a dose tapering phase started. The lowest dose of 1 mg used in Study 2 was not randomized to patients weighing more than 50 kg. Patients who weighed less than 25 kg were not included in either study.

Signs and symptoms of ADHD were evaluated on a once weekly basis using the clinician administered and scored ADHD Rating Scale (ADHD-RS-IV), which includes both hyperactive/impulsive and inattentive subscales. The primary efficacy outcome was the change from baseline to endpoint in ADHD-RS-IV total scores. Endpoint was defined as the last post-randomization treatment week for which a valid score was obtained prior to dose tapering (up to Week 5 in Study 1 and up to Week 6 in Study 2).

The mean reductions in ADHD-RS-IV total scores at endpoint were statistically significantly greater for INTUNIV compared to placebo for Studies 1 and 2. Placebo-adjusted changes from baseline were statistically significant for each of the 2 mg, 3 mg, and 4 mg INTUNIV randomized treatment groups in both studies, as well as the 1 mg INTUNIV treatment group that was included only in Study 2 (see Table 16).

Dose-responsive efficacy was evident, particularly when data were examined on a weight-adjusted (mg/kg) basis. When evaluated over the dose range of 0.01 to 0.17 mg/kg/day, clinically relevant improvements were observed beginning at doses in the range 0.05 to 0.08 mg/kg/day. Doses up to 0.12 mg/kg/day were shown to provide additional benefit.

In the monotherapy trials (Studies 1 and 2), subgroup analyses were performed to identify any differences in response based on gender or age (6 to 12 vs. 13 to 17). Analyses of the primary outcome did not suggest any differential responsiveness on the basis of gender. Analyses by age revealed a statistically significant treatment effect only in the 6 to 12 age subgroup. Due to the relatively small proportion of adolescent patients (ages 13 to 17) enrolled into these studies (approximately 25%), these data may not have been sufficient to demonstrate efficacy in the adolescent patients. In these studies, patients were randomized to a fixed dose of INTUNIV rather than optimized by body weight. Therefore, some adolescent patients were randomized to a dose that might have resulted in relatively lower plasma guanfacine concentrations compared to the younger patients. Over half (55%) of the adolescent patients received doses of 0.01 to 0.04 mg/kg. In studies in which systematic pharmacokinetic data were obtained, there was a strong inverse correlation between body weight and plasma guanfacine concentrations.

Table 16: Fixed dose Studies
Study Number (Age Range) | Treatment Group | Primary Efficacy Measure: ADHD-RS-IV Total Score
Study Number (Age Range) |  | Mean Baseline Score (SD) | LS Mean Change from Baseline (SE) | Placebo-subtracted Difference [Difference (drug minus placebo) in least-squares mean change from baseline.] (95% CI)
Study 1 (6 to 17 years) | INTUNIV 2 mg [Doses statistically significantly superior to placebo.] | 36.1 (9.99) | -15.9 (1.37) | -7.4 (-11.3, -3.5)
Study 1 (6 to 17 years) | INTUNIV 3 mg | 36.8 (8.72) | -16.0 (1.38) | -7.5 (-11.4, -3.6)
Study 1 (6 to 17 years) | INTUNIV 4 mg | 38.4 (9.21) | -18.5 (1.39) | -10.0 (-13.9, -6.1)
Study 1 (6 to 17 years) | Placebo | 38.1 (9.34) | -8.5 (1.42) | --
Study 2 (6 to 17 years) | INTUNIV 1 mg [The lowest dose of 1 mg used in Study 2 was not randomized to patients weighing more than 50 kg.] | 41.7 (7.81) | -19.4 (1.69) | -6.8 (-11.3, -2.2)
Study 2 (6 to 17 years) | INTUNIV 2 mg | 39.9 (8.74) | -18.1 (1.60) | -5.4 (-9.9, -0.9)
Study 2 (6 to 17 years) | INTUNIV 3 mg | 39.1 (9.22) | -20.0 (1.64) | -7.3 (-11.8, -2.8)
Study 2 (6 to 17 years) | INTUNIV 4 mg | 40.6 (8.57) | -20.6 (1.60) | -7.9 (-12.3, -3.4)
Study 2 (6 to 17 years) | Placebo | 39.3 (8.85) | -12.7 (1.60) | --
SD: standard deviation; SE: standard error; LS Mean: least-squares mean; CI: unadjusted confidence interval.

Study 3: Flexible-dose INTUNIV as Adjunctive Therapy to Psychostimulants

Study 3 (313 study) was a double-blind, randomized, placebo-controlled, dose-optimization study, in which efficacy of once daily optimized dosing (morning or evening) with INTUNIV (1 mg, 2 mg, 3 mg, and 4 mg), when co-administered with psychostimulants, was evaluated for 8 weeks, in children and adolescents aged 6 to 17 years with a diagnosis of ADHD, with a sub-optimal response to stimulants (n=455). Patients were started at the 1 mg INTUNIV dose level and were titrated weekly over a 5-week dose-optimization period to an optimal INTUNIV dose not to exceed 4 mg/day based on tolerability and clinical response. The dose was then maintained for a 3-week dose maintenance period before entry to 1 week of dose tapering. Patients took INTUNIV either in the morning or the evening while maintaining their current dose of psychostimulant treatment given each morning. Allowable psychostimulants in the study were ADDERALL XR®, VYVANSE®, CONCERTA®, FOCALIN XR®, RITALIN LA®, METADATE CD®, or FDA-approved generic equivalents.

Symptoms of ADHD were evaluated on a weekly basis by clinicians using the ADHD Rating Scale (ADHD-RS-IV), which includes both hyperactive/impulsive and inattentive subscales. The primary efficacy outcome was the change from baseline to endpoint in ADHD-RS-IV total scores. Endpoint was defined as the last post-randomization treatment week prior to dose tapering for which a valid score was obtained (up to Week 8).

Mean reductions in ADHD-RS-IV total scores at endpoint were statistically significantly greater for INTUNIV given in combination with a psychostimulant compared to placebo given with a psychostimulant for Study 3, for both morning and evening INTUNIV dosing (see Table 17). Nearly two-thirds (64.2%) of patients reached optimal doses in the 0.05 to 0.12 mg/kg/day range.

Studies 4, 5, and 6: Flexible-dose INTUNIV Monotherapy

Study 4 (314 study) was a double-blind, randomized, placebo-controlled, dose-optimization study, in which efficacy of once daily dosing (morning or evening) with INTUNIV (1 mg, 2 mg, 3 mg, and 4 mg) was evaluated for 8 weeks in children aged 6 to 12 years (n=340).

Signs and symptoms of ADHD were evaluated on a once weekly basis using the clinician administered and scored ADHD Rating Scale (ADHD-RS-IV), which includes both hyperactive/impulsive and inattentive subscales. The primary efficacy outcome was the change from baseline score at endpoint on the ADHD-RS-IV total scores. Endpoint was defined as the last post-randomization treatment week for which a valid score was obtained prior to dose tapering (up to Week 8).

Mean reductions in ADHD-RS-IV total scores at endpoint were statistically significantly greater for INTUNIV compared to placebo in both AM and PM dosing groups of INTUNIV (see Table 17).

Study 5 (312 study) was a 15-week, double-blind, randomized, placebo-controlled, dose-optimization study conducted in adolescents aged 13 to 17 years (n=314) to evaluate the efficacy and safety of INTUNIV (1 to 7 mg/day; optimized dose range of 0.05 to 0.12 mg/kg/day) in the treatment of ADHD as measured by the ADHD Rating Scale-IV (ADHD-RS-IV). Patients receiving INTUNIV showed statistically significantly greater improvement on the ADHD-RS-IV total score compared with patients receiving placebo (see Table 17).

Study 6 (316 study) was a 12-week (for children aged 6 to 12) or 15-week (for adolescents aged 13 to 17), randomized, double-blind, parallel-group, placebo- and active-reference, dose-optimization study conducted in pediatric patients (children and adolescents aged 6 to 17 years old inclusive) (n=337) to assess the efficacy and safety of once-daily dosing (children: 1 to 4 mg/day, adolescents: 1 to 7 mg/day; optimized dose range of 0.05 to 0.12 mg/kg/day) in the treatment of ADHD. INTUNIV was statistically superior to placebo on symptoms of ADHD in patients 6 to 17 years as measured by change from baseline in ADHD-RS-IV total scores (see Table 17).

Table 17: Flexible-Dose studies
Study Number (Age Range) | Treatment Group | Primary Efficacy Measure: ADHD-RS-IV Total Score
Study Number (Age Range) | Treatment Group | Mean Baseline Score (SD) | LS Mean Change from Baseline (SE) | Placebo-subtracted Difference [Difference (drug minus placebo) in least-squares mean change from baseline.] (95% CI)
Study 3 [Treatment was given in combination with a psychostimulant.] (6 to 17 years) | INTUNIV 1 to 4 mg AM [Doses statistically significantly superior to placebo.] | 37.6 (8.13) | -20.3 (0.97) | -4.5 (-7.5, -1.4)
Study 3 [Treatment was given in combination with a psychostimulant.] (6 to 17 years) | INTUNIV 1 to 4 mg PM | 37.0 (7.65) | -21.2 (0.97) | -5.3 (-8.3, -2.3)
Study 3 [Treatment was given in combination with a psychostimulant.] (6 to 17 years) | Placebo | 37.7 (7.75) | -15.9 (0.96) | --
Study 4 (6 to 12 years) | INTUNIV 1 to 4 mg AM | 41.7 (6.39) | -20.0 (1.23) | -9.4 (-12.8, -6.0)
Study 4 (6 to 12 years) | INTUNIV 1 to 4 mg PM | 41.6 (6.66) | -20.4 (1.19) | -9.8 (-13.1, -6.4)
Study 4 (6 to 12 years) | Placebo | 42.9 (6.29) | -10.6 (1.20) | --
Study 5 (13 to 17 years) | INTUNIV 1 to 7 mg | 39.9 (5.57) | -24.6 (1.06) | -6.03 (-8.87, -3.19)
Study 5 (13 to 17 years) | Placebo | 40.0 (6.11) | -18.5 (1.08) | --
Study 6 (6 to 17 years) | INTUNIV 1 to 7 mg | 43.1 (5.47) | -23.89 (1.15) | -8.88 (-11.94, -5.81)
Study 6 (6 to 17 years) | Placebo | 43.2 (5.60) | -15.01 (1.16) | --
SD: standard deviation; SE: standard error; LS Mean: least-squares mean; CI: unadjusted confidence interval.

Study 7: Long-Term Maintenance of INTUNIV Efficacy

Study 7 (315 study) was a double-blind, placebo-controlled, randomized withdrawal trial in pediatric patients aged 6 to 17 years with DSM-IV-TR diagnosis of ADHD. The study consisted of an open-label phase, including a 7-week dose optimization period to titrate patients to an optimal dose (maximum 4 mg/day for children and 7 mg/day for adolescents; optimized dose range: 0.05 to 0.12 mg/kg/day) and a 6-week dose maintenance period. There were 526 patients included in the open-label phase. Among those, 315 patients who met response criteria in the open-label phase were then randomized (1:1, INTUNIV:placebo) in a 26-week, double-blind, randomized withdrawal phase. The response criteria were defined by ≥30% reduction in ADHD-RS-IV total score and a Clinical Global Impression-Improvement (CGI-I) score of 1 or 2 during the open-label phase. A statistically significantly lower proportion of treatment failures occurred among INTUNIV patients compared to placebo at the end of the randomized withdrawal period (Figure 4). Treatment failure was defined as a ≥50% increase (worsening) in ADHD-RS-IV total score and a ≥2-point increase in Clinical Global Impression-Severity (CGI-S) score. Patients who met the treatment failure criteria on two consecutive visits or discontinued for any reason were classified as treatment failure.

Figure 4. Kaplan-Meier Estimation of Proportion of Patients with Treatment Failure for Children and Adolescents Ages 6 to 17 (Study 7)

16 HOW SUPPLIED/STORAGE AND HANDLING

INTUNIV is supplied in 1 mg, 2 mg, 3 mg, and 4 mg strength extended-release tablets in 100 count bottles.

 | 1 mg | 2 mg | 3 mg | 4 mg
Color | White/off-white | White/off-white | Green | Green
Shape | Round | Caplet | Round | Caplet
Debossment (top/bottom) | 503 / 1 mg | 503 / 2 mg | 503 / 3 mg | 503 / 4 mg
NDC number | 54092-513-02 | 54092-515-02 | 54092-517-02 | 54092-519-02

STORAGE AND HANDLING

Storage - Store at 20°C to 25°C (68°F to 77°F); excursions permitted to 15°C to 30°C (59°F to 86°F). See USP Controlled Room Temperature.

17 PATIENT COUNSELING INFORMATION

Advise the patient to read the FDA-approved patient labeling (Patient Information).

Dosing and Administration

Instruct patients to swallow INTUNIV whole with water, milk, or other liquid. Tablets should not be crushed, chewed or broken prior to administration because this may increase the rate of release of the active drug. Patients should not take INTUNIV together with a high-fat meal, since this can raise blood levels of INTUNIV. Instruct the parent or caregiver to supervise the child or adolescent taking INTUNIV and to keep the bottle of tablets out of reach of children.

Advise patients not to abruptly discontinue INTUNIV as abrupt discontinuation can result in clinically significant rebound hypertension. Concomitant stimulant use and abrupt discontinuation of INTUNIV may increase this hypertensive response. Instruct patients on how to properly taper the dose to minimize the risk of rebound hypertension [see Dosage and Administration (2.5) and Warnings and Precautions (5.4)].

Adverse Reactions

Advise patients that sedation can occur, particularly early in treatment or with dose increases. Caution against operating heavy equipment or driving until they know how they respond to treatment with INTUNIV [see Warnings and Precautions (5.2)]. Headache and abdominal pain can also occur. If any of these symptoms persist, or other symptoms occur, the patient should be advised to discuss the symptoms with the health care provider.

Advise patients to avoid becoming dehydrated or overheated, which may potentially increase the risks of hypotension and syncope [see Warnings and Precautions (5.1)]. Advise patients to avoid use with alcohol.

Pregnancy Registry

Advise patients that there is a pregnancy exposure registry that monitors pregnancy outcomes in patients exposed to INTUNIV during pregnancy [see Use in Specific Populations (8.1)].

Lactation

Advise breastfeeding mothers to monitor infants exposed to guanfacine through breastmilk for sedation, lethargy, and poor feeding [see Use in Specific Populations (8.2)].

Patient Information

INTUNIV® (in-TOO-niv)
(guanfacine)
Extended-Release Tablets

Read the Patient Information that comes with INTUNIV before you start taking it and each time you get a refill. There may be new information. This leaflet does not take the place of talking with your doctor about your medical condition or your treatment.

What is INTUNIV?

INTUNIV is a prescription medicine used to treat the symptoms of attention deficit hyperactivity disorder (ADHD). INTUNIV may be used alone or with ADHD stimulant medicines.

INTUNIV is not a central nervous system (CNS) stimulant.

It is not known if INTUNIV is safe and effective in children younger than 6 years of age.

Who should not take INTUNIV?

Do not take INTUNIV if you are allergic to guanfacine or any of the ingredients in INTUNIV. See the end of this leaflet for a complete list of ingredients in INTUNIV.

What should I tell my doctor before taking INTUNIV?

Before you take INTUNIV, tell your doctor if you:

- have heart problems or a low heart rate
- have fainted
- have low or high blood pressure
- have liver or kidney problems
- have any other medical conditions
- are pregnant or plan to become pregnant. It is not known if INTUNIV will harm your unborn baby. Talk to your doctor if you are pregnant or plan to become pregnant.
  - There is a pregnancy registry for females who are exposed to ADHD medications, including INTUNIV, during pregnancy. The purpose of the registry is to collect information about the health of females exposed to INTUNIV and their baby. If you or your child becomes pregnant during treatment with INTUNIV, talk to your healthcare provider about registering with the National Pregnancy Registry of ADHD medications at 1-866-961-2388.
- are breastfeeding or plan to breastfeed. It is not known if INTUNIV passes into your breast milk. Talk to your doctor about the best way to feed your baby while taking INTUNIV.

Tell your doctor about all of the medicines you take, including prescription and over-the-counter medicines, vitamins, and herbal supplements.

INTUNIV may affect the way other medicines work, and other medicines may affect how INTUNIV works.

Especially tell your doctor if you take:

- ketoconazole
- medicines that can affect enzyme metabolism
- high blood pressure medicine
- sedatives
- benzodiazepines
- barbiturates
- antipsychotics

Ask your doctor or pharmacist for a list of these medicines, if you are not sure.

Know the medicines you take. Keep a list of them and show it to your doctor and pharmacist when you get a new medicine.

How should I take INTUNIV?

- Take INTUNIV exactly as your doctor tells you.
- Your doctor may change your dose. Do not change your dose of INTUNIV without talking to your doctor.
- Do not stop taking INTUNIV without talking to your doctor.
- Try not to miss your dose of INTUNIV. If you miss a dose of INTUNIV, take the next dose at your regular time. If you miss 2 or more doses, talk to your doctor, as you may need to restart INTUNIV with a lower dose.
- Do not take a double dose to make up for a missed dose.
- INTUNIV should be taken 1 time a day in the morning or in the evening, either alone or in combination with an ADHD stimulant medicine that your doctor may prescribe. Your doctor will tell you when to take INTUNIV and when to take your ADHD stimulant medication.
- INTUNIV should be swallowed whole with a small amount of water, milk, or other liquid.
- Do not crush, chew, or break INTUNIV. Tell your doctor if you cannot swallow INTUNIV whole.
- Do not take INTUNIV with a high-fat meal.
- Your doctor will check your blood pressure and heart rate while you take INTUNIV.
- If you take too much INTUNIV, call your local Poison Control Center at 1-800-222-1222 or go to the nearest emergency room right away.

What should I avoid while taking INTUNIV?

- Do not drive, operate heavy machinery, or do other dangerous activities until you know how INTUNIV affects you. INTUNIV can slow your thinking and motor skills.
- Do not drink alcohol or take other medicines that make you sleepy or dizzy while taking INTUNIV until you talk with your doctor. INTUNIV taken with alcohol or medicines that cause sleepiness or dizziness may make your sleepiness or dizziness worse.
- Do not become dehydrated or overheated. This may increase your chance of having low blood pressure or fainting while taking INTUNIV.
- Do not suddenly stop INTUNIV. Tell your healthcare provider if you have been vomiting and cannot take INTUNIV, you may be at risk for rebound hypertension.

What are the possible side effects of INTUNIV?

INTUNIV may cause serious side effects including:

- low blood pressure
- low heart rate
- fainting
- sleepiness
- increased blood pressure and heart rate after suddenly stopping INTUNIV (rebound hypertension). Suddenly stopping INTUNIV can cause increased blood pressure and heart rate and other withdrawal symptoms such as headache, confusion, nervousness, agitation, and tremors. If these symptoms continue to get worse and are left untreated, it could lead to a very serious condition including very high blood pressure, feeling very sleepy or tired, severe headache, vomiting, vision problems, seizures.

Get medical help right away, if you have any of the symptoms listed above.

The most common side effects of INTUNIV include:

- sleepiness
- tiredness
- trouble sleeping
- low blood pressure
- nausea
- stomach pain
- dizziness
- dry mouth
- irritability
- vomiting
- slow heart rate

Tell the doctor if you have any side effect that bothers you or that does not go away.

These are not all the possible side effects of INTUNIV. For more information, ask your doctor or pharmacist.

Call your doctor for medical advice about side effects. You may report side effects to FDA at 1-800-FDA-1088.

How should I store INTUNIV?

- Store INTUNIV between 68°F to 77°F (20°C to 25°C)

Keep INTUNIV and all medicines out of the reach of children.

General Information about the safe and effective use INTUNIV

Medicines are sometimes prescribed for purposes other than those listed in a Patient Information Leaflet. Do not use INTUNIV for a condition for which it was not prescribed. Do not give INTUNIV to other people, even if they have the same symptoms that you have. It may harm them.

This leaflet summarizes the most important information about INTUNIV. If you would like more information, talk with your doctor. You can ask your pharmacist or doctor for information about INTUNIV that is written for health professionals.

For more information, go to www.INTUNIV.com or call 1-877-825-3327.

What are the ingredients in INTUNIV?

Active ingredient: guanfacine hydrochloride

Inactive ingredients: hypromellose, methacrylic acid copolymer, lactose, povidone, crospovidone, microcrystalline cellulose, fumaric acid, and glycerol behenate. In addition, the 3 mg and 4 mg tablets also contain green pigment blend PB-1763.

This Patient Information has been approved by the U.S. Food and Drug Administration.

Distributed by:
Takeda Pharmaceuticals America, Inc.
Cambridge, MA 02142

INTUNIV is a registered trademark of Takeda Pharmaceuticals U.S.A., Inc.

© 2025 Takeda Pharmaceuticals U.S.A., Inc. All rights reserved.

Patented: see www.takeda.com/en-us/patents.

Revised: 6/2025

PRINCIPAL DISPLAY PANEL - 1 mg Tablet Bottle Label

NDC 54092-513-02

intuniv®
(guanfacine)
Extended-Release Tablets

100 Tablets
1 mg
Rx only

Each tablet contains: 1 mg of guanfacine, as guanfacine HCl

Tablets should not be crushed,
chewed or broken before swallowing.

Distributed by:
Takeda Pharmaceuticals
America, Inc.
Cambridge, MA 02142

Takeda

Product of Spain

PRINCIPAL DISPLAY PANEL - 2 mg Tablet Bottle Label

NDC 54092-515-02

intuniv®
(guanfacine)
Extended-Release Tablets

100 Tablets
2 mg
Rx only

Each tablet contains: 2 mg of guanfacine, as guanfacine HCl

Tablets should not be crushed,
chewed or broken before swallowing.

Distributed by:
Takeda Pharmaceuticals
America, Inc.
Cambridge, MA 02142

Takeda

Product of Spain

PRINCIPAL DISPLAY PANEL - 3 mg Tablet Bottle Label

NDC 54092-517-02

intuniv®
(guanfacine)
Extended-Release Tablets

100 Tablets
3 mg
Rx only

Each tablet contains: 3 mg of guanfacine, as guanfacine HCl

Tablets should not be crushed,
chewed or broken before swallowing.

Distributed by:
Takeda Pharmaceuticals
America, Inc.
Cambridge, MA 02142

Takeda

Product of Spain

PRINCIPAL DISPLAY PANEL - 4 mg Tablet Bottle Label

NDC 54092-519-02

intuniv®
(guanfacine)
Extended-Release Tablets

100 Tablets
4 mg
Rx only

Each tablet contains: 4 mg of guanfacine, as guanfacine HCl

Tablets should not be crushed,
chewed or broken before swallowing.

Distributed by:
Takeda Pharmaceuticals
America, Inc.
Cambridge, MA 02142

Takeda

Product of Spain

PRINCIPAL DISPLAY PANEL - NDC 54092-520-01

Image not Available